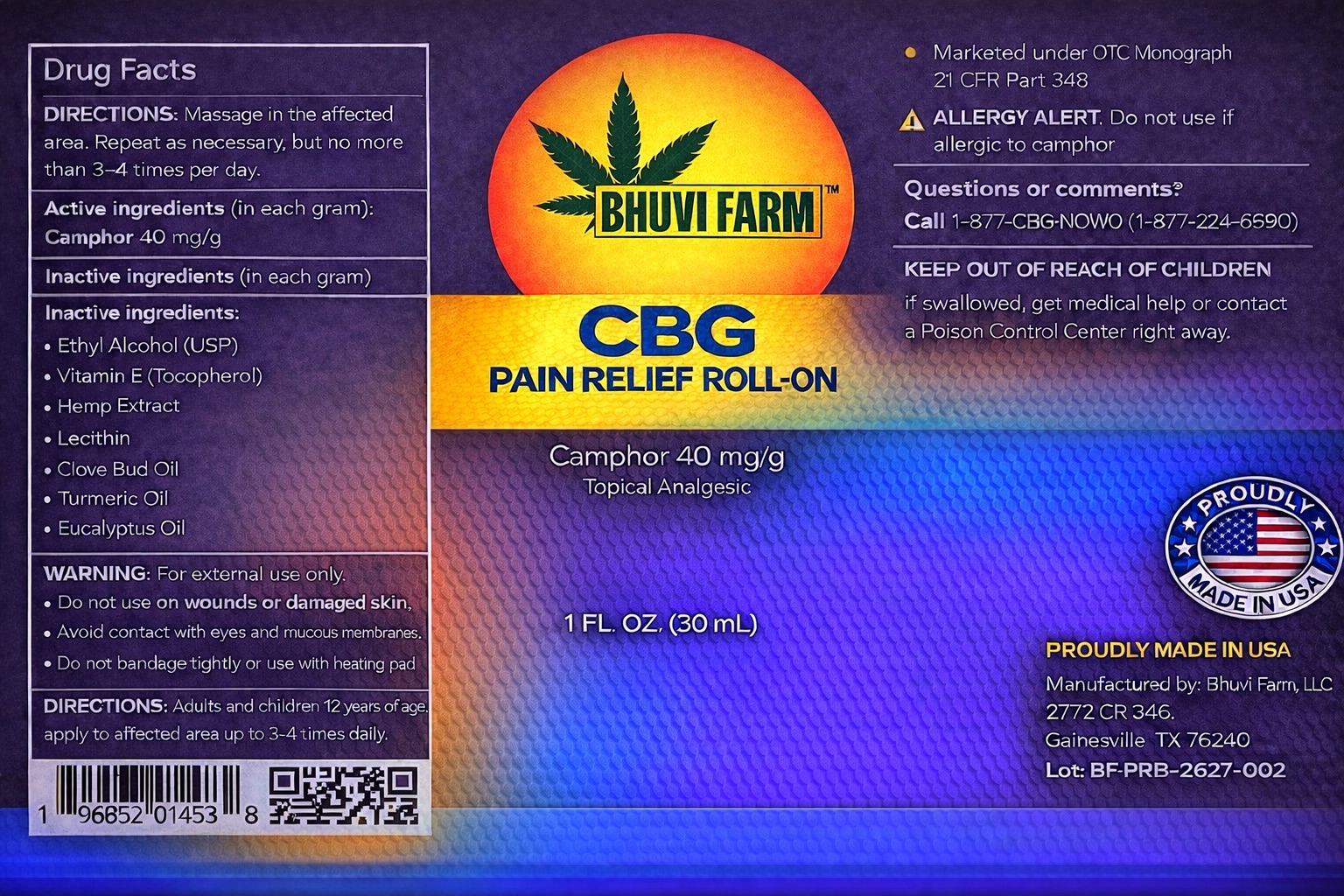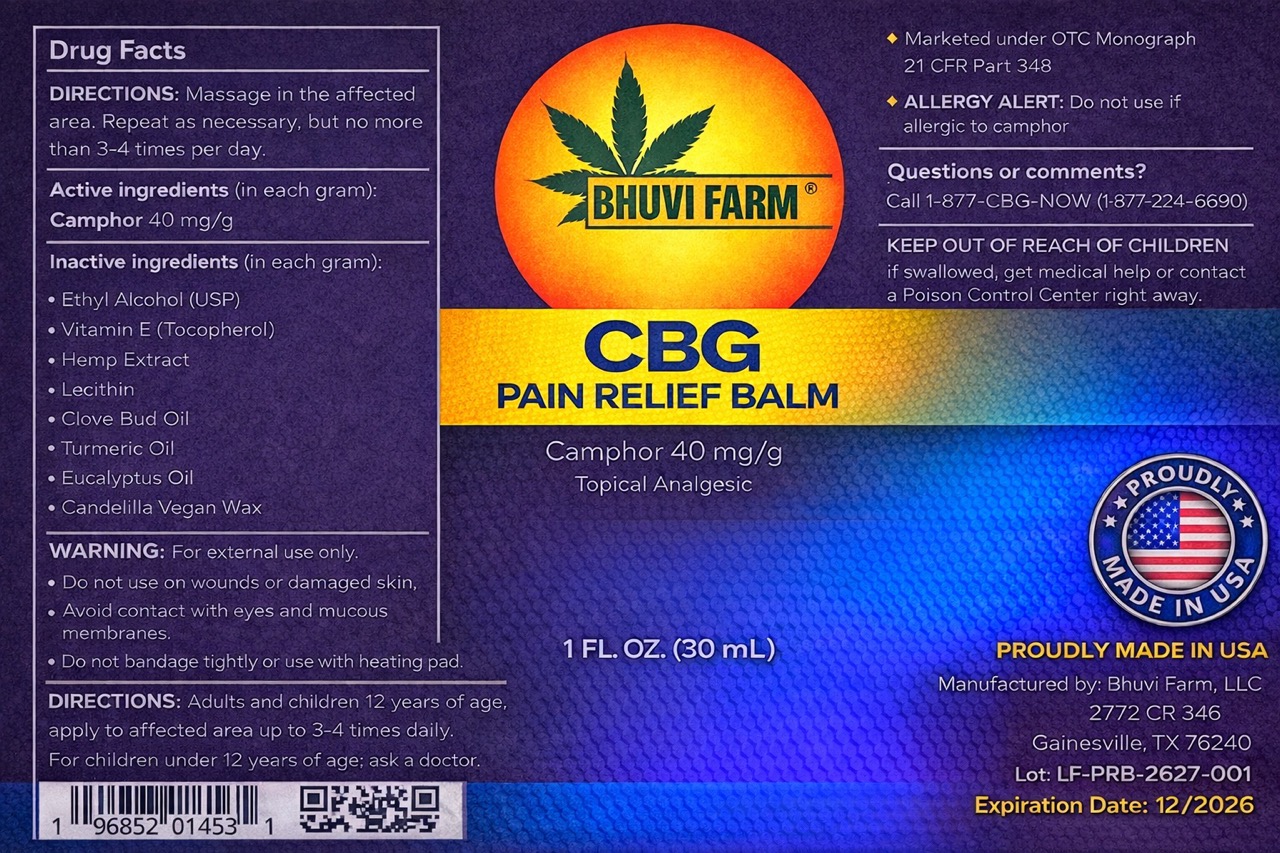 DRUG LABEL: CBG PAIN RELIEF BALM
NDC: 87423-101 | Form: SALVE
Manufacturer: JAWAHAR MIRYALA
Category: otc | Type: HUMAN OTC DRUG LABEL
Date: 20260210

ACTIVE INGREDIENTS: CAMPHOR (NATURAL) 40 mg/1 g
INACTIVE INGREDIENTS: .ALPHA.-TOCOPHEROL 4.37 mg/1 g

temporarily relieves minor aches and pains of muscles and joints associated with: • simple backache • arthritis • strains • bruises • sprains

temporarily relieves minor aches and pains of muscles and joints

Inactive ingredients

Inactive ingredientsEthyl Alcohol (USP),

Tocopherol,

Hemp Extract,

Lecithin,

Clove Bud Oil,
Turmeric Oil,

Eucalyptus Oil

External analgesic

For external use only.

Do not use
• on wounds or damaged skin
• with a heating pad

When using this product
• avoid contact with eyes or mucous membranes
• do not bandage tightly

Stop use and ask a doctor if
• condition worsens
• symptoms persist for more than 7 days or clear up and occur again within a few days

If pregnant or breast-feeding,
ask a health professional before use.

Keep out of reach of children. If swallowed, get medical help or contact a Poison Control Center right away.

Keep out of reach of children.
If swallowed, get medical help or contact a Poison Control Center right away.

Directions adults and children 12 years and older: apply to affected area not more than 3 to 4 times daily children under 12 years: consult a doctor

Directions
adults and children 12 years and older:
apply to affected area not more than 3 to 4 times daily

children under 12 years:
consult a doctor

CBG Pain Relief Balm – Immediate Container Label